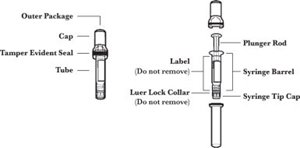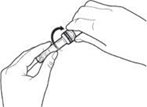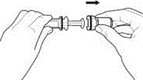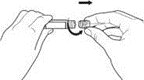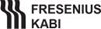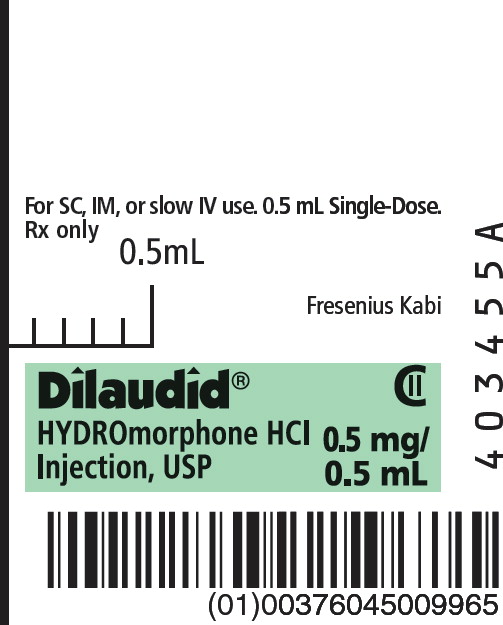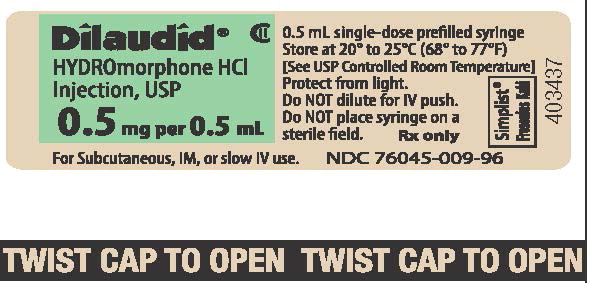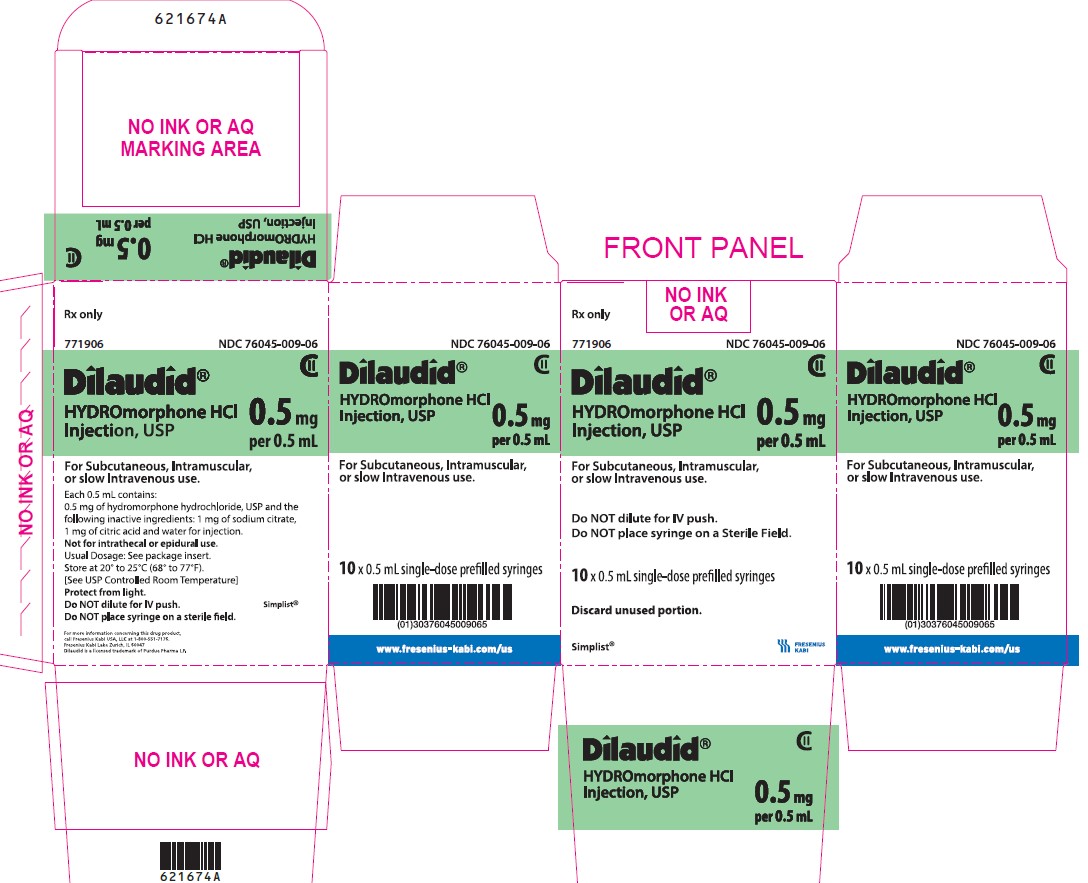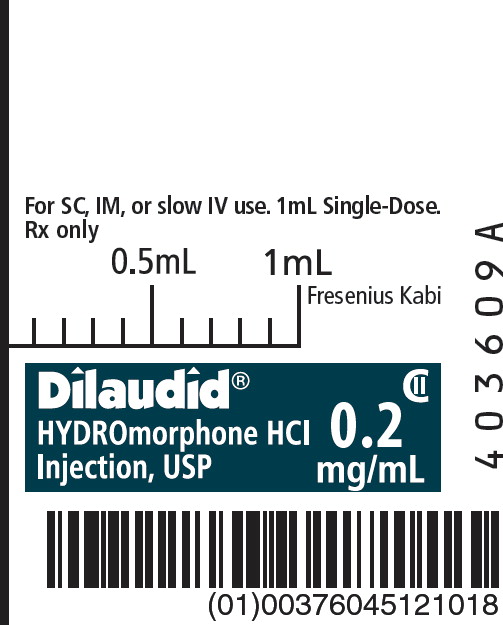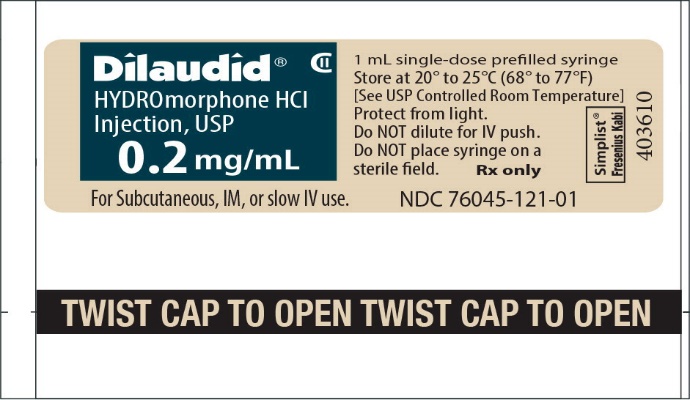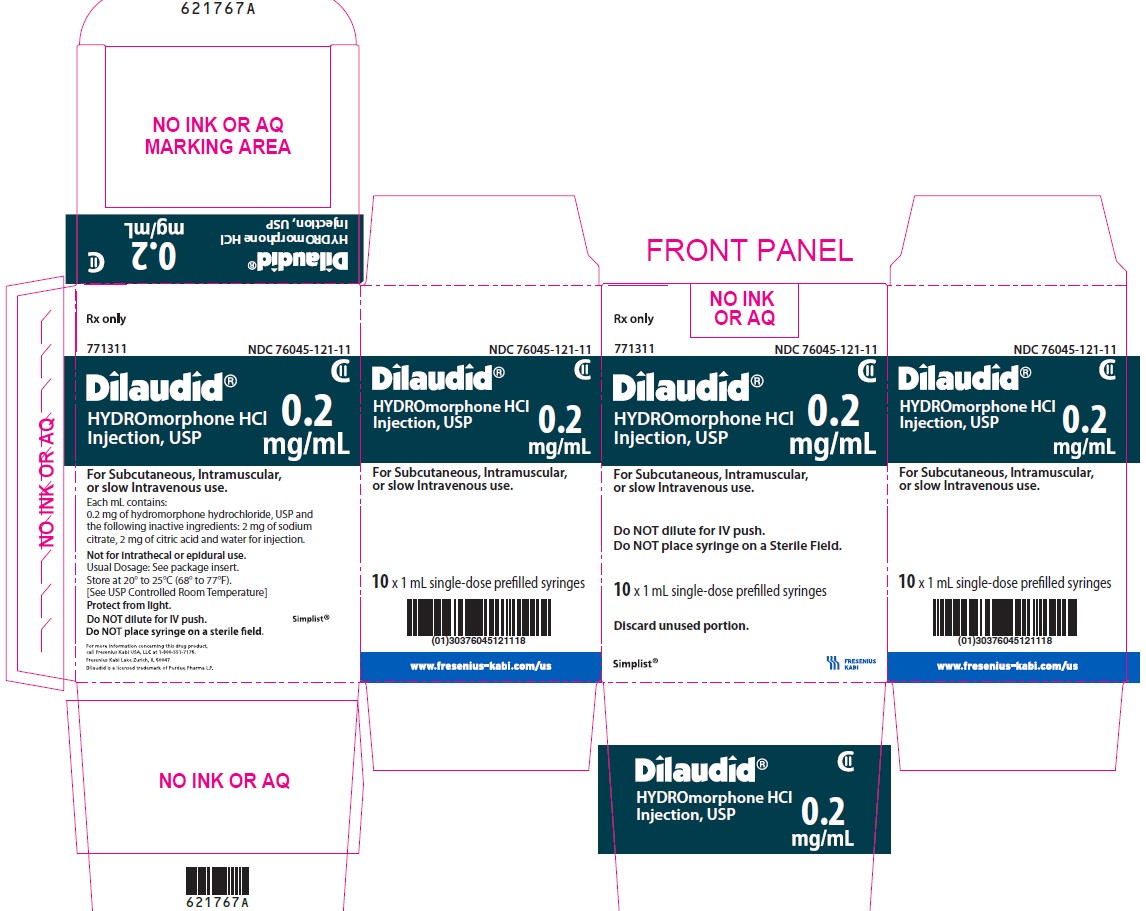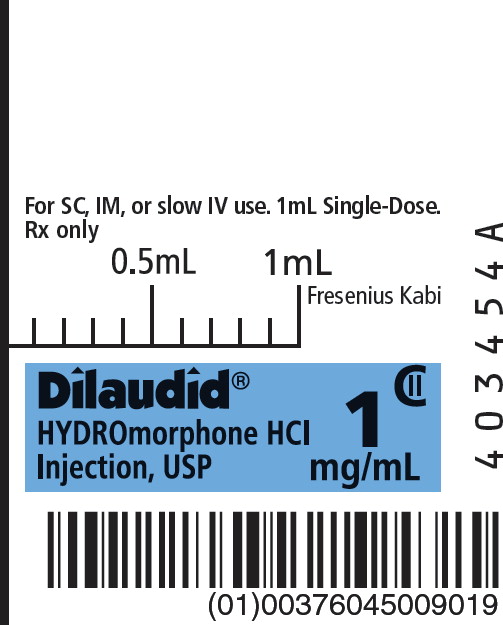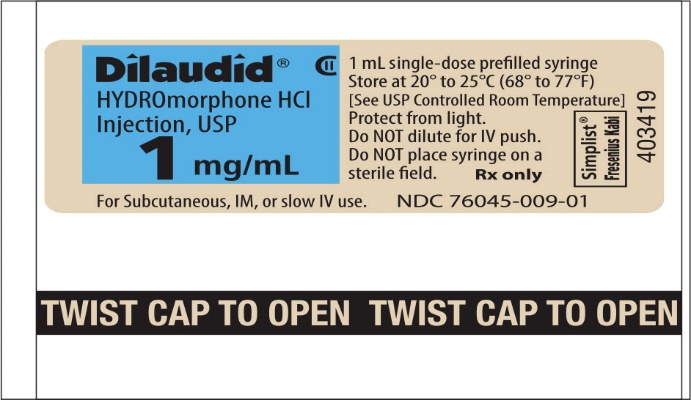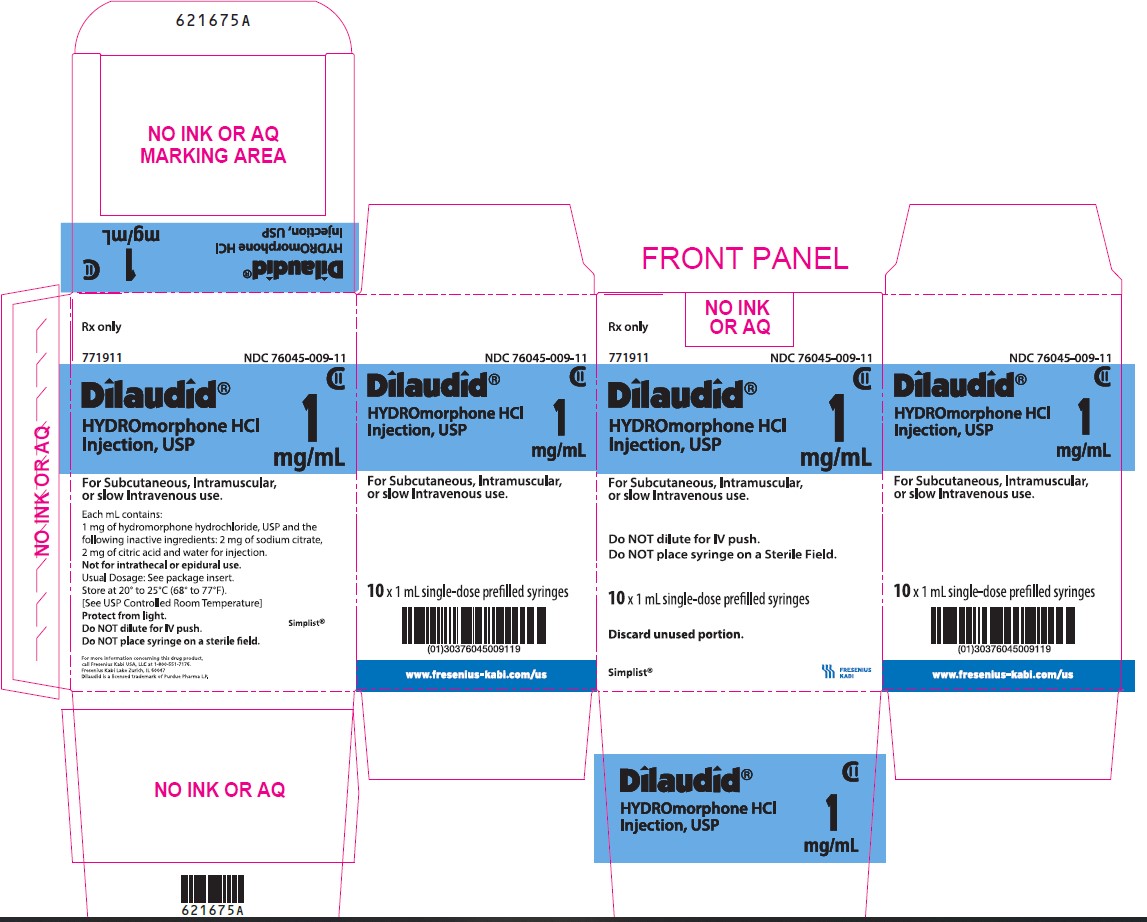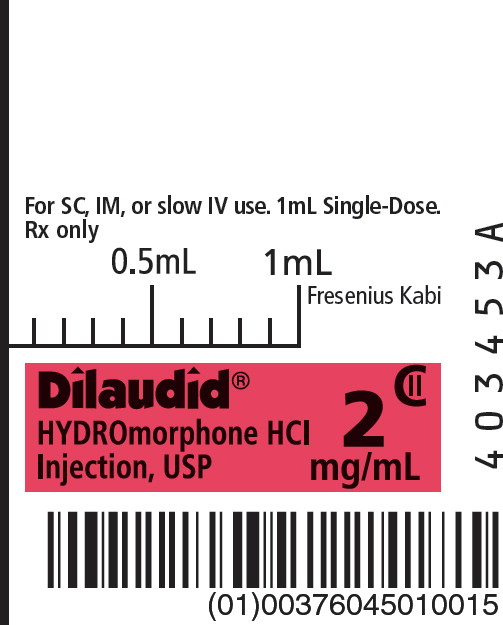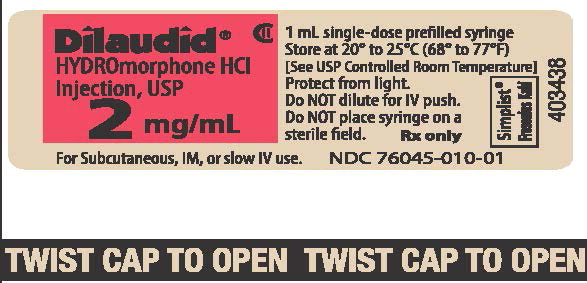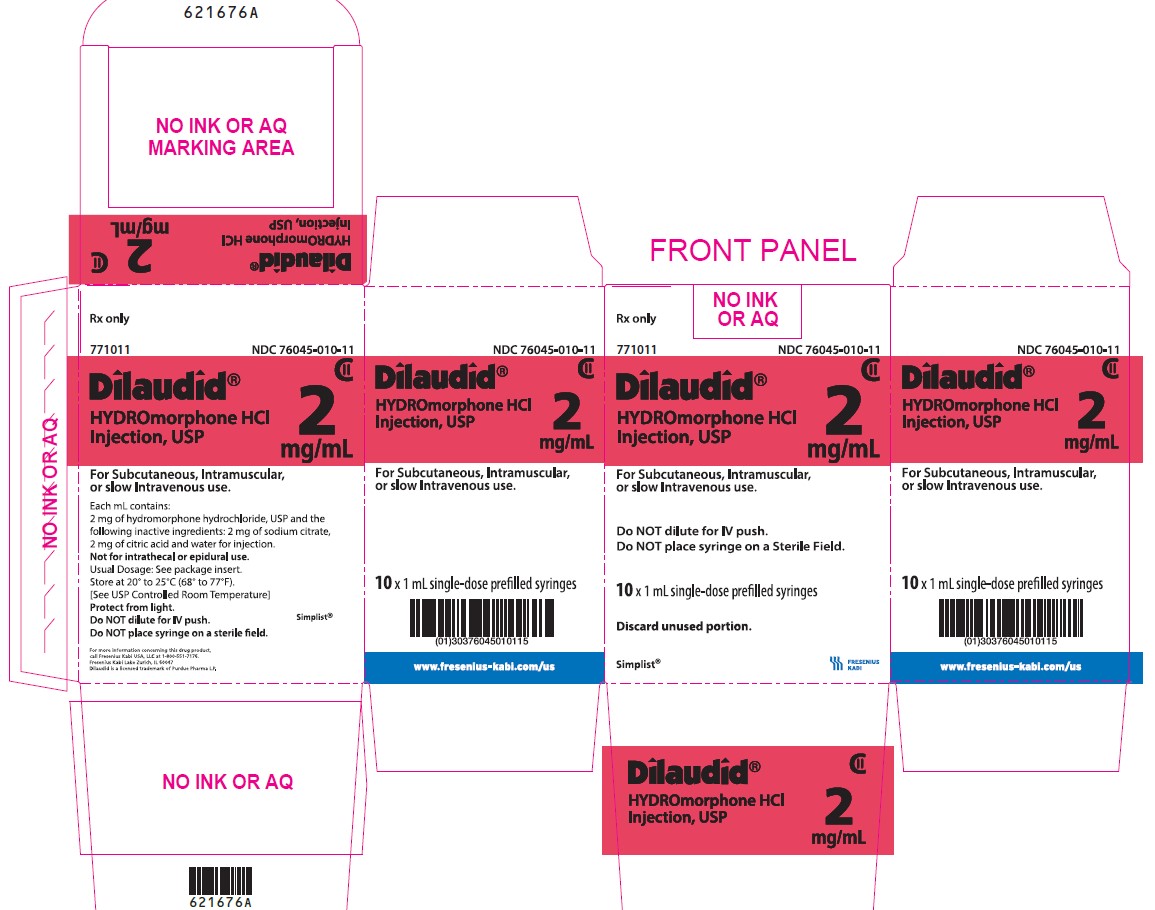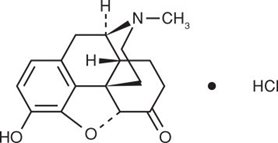 DRUG LABEL: Dilaudid
NDC: 76045-009 | Form: INJECTION, SOLUTION
Manufacturer: Fresenius Kabi USA, LLC
Category: prescription | Type: HUMAN PRESCRIPTION DRUG LABEL
Date: 20250428
DEA Schedule: CII

ACTIVE INGREDIENTS: HYDROMORPHONE HYDROCHLORIDE 1 mg/1 mL
INACTIVE INGREDIENTS: SODIUM CITRATE, UNSPECIFIED FORM; CITRIC ACID MONOHYDRATE; WATER

HIGHLIGHTS OF PRESCRIBING INFORMATION

These highlights do not include all the information needed to use DILAUDID® INJECTION safely and effectively.
See full prescribing information for DILAUDID® INJECTION.
DILAUDID® INJECTION (hydromorphone hydrochloride) for intravenous, intramuscular, or subcutaneous use, CII
Initial U.S. Approval: January 1984

RECENT MAJOR CHANGES

Boxed Warning 12/2023

Indications and Usage (1) 12/2023

Dosage and Administration (2.1, 2.2, 2.5) 12/2023

Warnings and Precautions (5.5) 12/2023

WARNING: SERIOUS AND LIFE-THREATENING RISKS FROM USE OF DILAUDID INJECTION

See full prescribing information for complete boxed warning.

- DILAUDID INJECTION exposes users to risks of addiction, abuse, and misuse, which can lead to overdose and death. Assess patient's risk before prescribing and reassess regularly for these behaviors and conditions. (5.1)
- Serious, life-threatening, or fatal respiratory depression may occur. Monitor closely, especially upon initiation or following a dosage increase. To reduce the risk of respiratory depression, proper dosing and titration of DILAUDID INJECTION are essential. (5.2)
- Concomitant use of opioids with benzodiazepines or other central nervous system (CNS) depressants, including alcohol, may result in profound sedation, respiratory depression, coma, and death. Reserve concomitant prescribing for use in patients for whom alternative treatment options are inadequate. (5.3, 7).
- If opioid use is required for an extended period of time in a pregnant woman, advise the patient of the risk of Neonatal Opioid Withdrawal Syndrome, which may be life-threatening if not recognized and treated. Ensure that management by neonatology experts will be available at delivery. (5.4).

1 INDICATIONS AND USAGE

DILAUDID INJECTION is an opioid agonist indicated for the management of pain severe enough to require an opioid analgesic and for which alternate treatments are inadequate. (1)

Limitations of Use: (1)

Because of the risks of addiction, abuse, and misuse with opioids, which can occur at any dosage or duration, reserve Hydromorphone Hydrochloride Injection for use in patients for whom alternative treatment options (e.g., non-opioid analgesics or opioid combination products):

- Have not been tolerated, or are not expected to be tolerated
- Have not provided adequate analgesia or are not expected to provide adequate analgesia

DILAUDID INJECTION should not be used for an extended period of time unless the pain remains severe enough to require an opioid analgesic and for which alternative treatment options continue to be inadequate.

2 DOSAGE AND ADMINISTRATION

- DILAUDID INJECTION should be prescribed only by healthcare professionals who are knowledgeable about the use of opioids and how to mitigate the associated risks. (2.1)
- Use the lowest effective dosage for the shortest duration of time consistent with individual patient treatment goals. Reserve titration to higher doses of Hydromorphone Hydrochloride Injection for patients in whom lower doses are insufficiently effective and in whom the expected benefits of using a higher dose opioid clearly outweigh the substantial risks. (2.1, 5)
- Many acute pain conditions (e.g., the pain that occurs with a number of surgical procedures or acute musculoskeletal injuries) require no more than a few days of an opioid analgesic. Clinical guidelines on opioid prescribing for some acute pain conditions are available. (2.1)
- Initiate the dosing regimen for each patient individually, taking into account the patient’s underlying cause and severity of pain, prior analgesic treatment and response, and risk factors for addiction, abuse, and misuse. (2.1, 5.1)
- Respiratory depression can occur at any time during opioid therapy, especially when initiating and following dosage increases with Hydromorphone Hydrochloride Injection. Consider this risk when selecting an initial dose and when making dose adjustments. (2.1, 5.2)
- Initial Dosage:
  - Intramuscular or Subcutaneous Use: The usual starting dose is 1 mg to 2 mg every 2 to 3 hours as necessary. (2.2)
  - Intravenous Use: The usual starting dose is 0.2 mg to 1 mg every 2 to 3 hours. The injection should be given slowly, over at least 2 to 3 minutes. (2.2)
- Hepatic Impairment: Initiate treatment with one-fourth to one-half the usual starting dose, depending on degree of hepatic impairment. (2.3)
- Renal Impairment: Initiate treatment with one-fourth to one-half the usual starting dose, depending on degree of renal impairment. (2.4)
- Do not abruptly discontinue DILAUDID INJECTION in a physically-dependent patient. (2.6, 5.12)

3 DOSAGE FORMS AND STRENGTHS

- DILAUDID Injection, 0.2 mg/mL, 0.5 mg/0.5 mL, 1 mg/mL or 2 mg/mL are available in single-dose prefilled syringes. (3)

4 CONTRAINDICATIONS

- Significant respiratory depression. (4)
- Acute or severe bronchial asthma in an unmonitored setting or in absence of resuscitative equipment. (4)
- Known or suspected gastrointestinal obstruction, including paralytic ileus. (4)
- Known hypersensitivity to hydromorphone, hydromorphone salts, sulfite-containing medications, or any other components of the product. (4)

5 WARNINGS AND PRECAUTIONS

- Opioid-Induced Hyperalgesia and Allodynia: Opioid-Induced Hyperalgesia (OIH) occurs when an opioid analgesic paradoxically causes an increase in pain, or an increase in sensitivity to pain. If OIH is suspected, carefully consider appropriately decreasing the dose of the current opioid analgesic, or opioid rotation. (5.5)
- Life-Threatening Respiratory Depression in Patients with Chronic Pulmonary Disease or in Elderly, Cachectic, or Debilitated Patients: Monitor closely, particularly during initiation and titration. (5.6)
- Adrenal Insufficiency: If diagnosed, treat with physiologic replacement of corticosteroids, and wean patient off of the opioid. (5.7)
- Severe Hypotension: Monitor during dosage initiation and titration. Avoid use of DILAUDID INJECTION in patients with circulatory shock. (5.8)
- Risks of Use in Patients with Increased Intracranial Pressure, Brain Tumors, Head Injury, or Impaired Consciousness: Monitor for sedation and respiratory depression. Avoid use of DILAUDID INJECTION in patients with impaired consciousness or coma. (5.9)
- DILAUDID INJECTION contains sodium metabisulfite. There is a risk of anaphylactic symptoms and life-threatening asthmatic episodes in susceptible people. (5.14)

6 ADVERSE REACTIONS

Most common adverse reactions are lightheadedness, dizziness, sedation, nausea, vomiting, sweating, flushing, dysphoria, euphoria, dry mouth, and pruritus. (6)

To report SUSPECTED ADVERSE REACTIONS, contact Fresenius Kabi USA, LLC at 1-800-551-7176 or FDA at 1-800-FDA-1088 or www.fda.gov/medwatch.

7 DRUG INTERACTIONS

- Serotonergic Drugs: Concomitant use may result in serotonin syndrome. Discontinue DILAUDID INJECTION if serotonin syndrome is suspected. (7)
- Monoamine Oxidase Inhibitors (MAOIs): Can potentiate the effects of hydromorphone. Avoid concomitant use in patients receiving MAOIs or within 14 days of stopping treatment with an MAOI. (7)
- Mixed Agonist/Antagonist and Partial Agonist Opioid Analgesics: Avoid use with DILAUDID INJECTION because they may reduce analgesic effect of DILAUDID INJECTION or precipitate withdrawal symptoms. (7)

8 USE IN SPECIFIC POPULATIONS

- Pregnancy: May cause fetal harm. (8.1)

FULL PRESCRIBING INFORMATION

WARNING: SERIOUS AND LIFE-THREATENING RISKS FROM USE OF DILAUDID INJECTION

Addiction, Abuse, and Misuse

Because the use of DILAUDID INJECTION exposes patients and other users to the risks of opioid addiction, abuse, and misuse, which can lead to overdose and death, assess each patient's risk prior to prescribing and reassess all patients regularly for the development of these behaviors and conditions [see Warnings and Precautions (5.1)].

Life-Threatening Respiratory Depression

Serious, life-threatening, or fatal respiratory depression may occur with use of DILAUDID INJECTION, especially during initiation or following a dosage increase. To reduce the risk of respiratory depression, proper dosing and titration of DILAUDID INJECTION are essential [see Warnings and Precautions (5.2)].

Risks From Concomitant Use With Benzodiazepines Or Other CNS Depressants

Concomitant use of opioids with benzodiazepines or other central nervous system (CNS) depressants, including alcohol, may result in profound sedation, respiratory depression, coma, and death. Reserve concomitant prescribing of DILAUDID INJECTION and benzodiazepines or other CNS depressants for use in patients for whom alternative treatment options are inadequate [see Warnings and Precautions (5.3), Drug Interactions (7)].

Neonatal Opioid Withdrawal Syndrome (NOWS)

If opioid use is required for an extended period of time in a pregnant woman, advise the patient of the risk of NOWS, which may be life-threatening if not recognized and treated. Ensure that management by neonatology experts will be available at delivery [see Warnings and Precautions (5.4)].

1 INDICATIONS AND USAGE

DILAUDID INJECTION is indicated for the management of pain severe enough to require an opioid analgesic and for which alternate treatments are inadequate.

Limitations of Use:

Because of the risks of addiction, abuse, and misuse with opioids, which can occur at any dosage or duration [see Warnings and Precautions (5.1)], reserve DILAUDID INJECTION for use in patients for whom alternative treatment options (e.g., non-opioid analgesics or opioid combination products):

- Have not been tolerated or are not expected to be tolerated,
- Have not provided adequate analgesia or are not expected to provide adequate analgesia.

DILAUDID INJECTION should not be used for an extended period of time unless the pain remains severe enough to require an opioid analgesic and for which alternative treatment options continue to be inadequate.

2 DOSAGE AND ADMINISTRATION

2.1 Important Dosage and Administration Instructions

- DILAUDID INJECTION should be prescribed only by healthcare professionals who are knowledgeable about the use of opioids and how to mitigate the associated risks.
- Use the lowest effective dosage for the shortest duration of time consistent with individual patient treatment goals [see Warnings and Precautions (5)]. Because the risk of overdose increases as opioid doses increase, reserve titration to higher doses of DILAUDID INJECTION for patients in whom lower doses are insufficiently effective and in whom the expected benefits of using a higher dose opioid clearly outweigh the substantial risks.
- Many acute pain conditions (e.g., the pain that occurs with a number of surgical procedures or acute musculoskeletal injuries) require no more than a few days of an opioid analgesic. Clinical guidelines on opioid prescribing for some acute pain conditions are available.
- There is variability in the opioid analgesic dose and duration needed to adequately manage pain due both to the cause of pain and to individual patient factors. Initiate the dosing regimen for each patient individually, taking into account the patient’s underlying cause and severity of pain, prior analgesic treatment and response, and risk factors for addiction, abuse, and misuse [see Warnings and Precautions (5.1)].
- Respiratory depression can occur at any time during opioid therapy, especially when initiating and following dosage increases with DILAUDID INJECTION. Consider this risk when selecting an initial dose and when making dose adjustments [see Warnings and Precautions (5)].
- Inspect parenteral drug products visually for particulate matter and discoloration prior to administration, whenever solution and container permit. A slight yellowish discoloration may develop in DILAUDID INJECTION. No loss of potency has been demonstrated. DILAUDID INJECTION is physically compatible and chemically stable for at least 24 hours at 25°C, protected from light in most common large-volume parenteral solutions.
- Discard any unused portion in an appropriate manner.

2.2 Initial Dosage

Use of DILAUDID INJECTION as the First Opioid Analgesic:

Subcutaneous or Intramuscular Administration:

The usual starting dose is 1 mg to 2 mg every 2 to 3 hours as necessary for pain, and the lowest dose necessary to achieve adequate analgesia. Depending on the clinical situation, the initial starting dose may be lowered in patients who are opioid naïve. Titrate the dose based upon the individual patient’s response to their initial dose of Hydromorphone Hydrochloride Injection.

Intravenous Administration:

The initial starting dose is 0.2 mg to 1 mg every 2 to 3 hours. Intravenous administration should be given slowly, over at least 2 to 3 minutes, depending on the dose. The initial dose should be reduced in the elderly or debilitated and may be lowered to 0.2 mg.

Conversion From Other Opioids to DILAUDID INJECTION:

There is inter-patient variability in the potency of opioid drugs and opioid formulations. Therefore, a conservative approach is advised when determining the total daily dosage of DILAUDID INJECTION. It is safer to underestimate a patient's 24-hour DILAUDID INJECTION dosage than to overestimate the 24-hour DILAUDID INJECTION dosage and manage an adverse reaction due to overdose.

If the decision is made to convert to Hydromorphone Hydrochloride Injection from another opioid analgesic using publicly available data, convert the current total daily amount(s) of opioid(s) received to an equivalent total daily dose of DILAUDID INJECTION and reduce by one-half due to the possibility of incomplete cross tolerance. Divide the new total amount by the number of doses permitted based on dosing interval (e.g., 8 doses for every- three-hour dosing). Titrate the dose according to the patient's response.

2.3 Dosage Modifications in Patients with Hepatic Impairment

Start patients with hepatic impairment on one-fourth to one-half the usual DILAUDID INJECTION starting dose depending on the extent of impairment [see Clinical Pharmacology (12.3)].

2.4 Dosage Modifications in Patients with Renal Impairment

Start patients with renal impairment on one-fourth to one-half the usual DILAUDID INJECTION starting dose depending on the degree of impairment [see Clinical Pharmacology (12.3)].

2.5 Titration and Maintenance of Therapy

Titrate the dose based upon the individual patient’s response to their initial dose of DILAUDID INJECTION. Individually titrate DILAUDID INJECTION to a dose that provides adequate analgesia and minimizes adverse reactions. Continually reevaluate patients receiving DILAUDID INJECTION to assess the maintenance of pain control, signs and symptoms of opioid withdrawal, and other adverse reactions, as well as monitoring for the development of addiction, abuse, or misuse [see Warnings and Precautions (5.1, 5.12)]. Frequent communication is important among the prescriber, other members of the healthcare team, the patient, and the caregiver/family during periods of changing analgesic requirements, including initial titration.

If the level of pain increases after dosage stabilization, attempt to identify the source of increased pain before increasing the DILAUDID INJECTION dosage. If after increasing the dosage, unacceptable opioid-related adverse reactions are observed (including an increase in pain after a dosage increase), consider reducing the dosage [see Warnings and Precautions (5)]. Adjust the dosage to obtain an appropriate balance between management of pain and opioid-related adverse reactions.

2.6 Safe Reduction or Discontinuation of DILAUDID INJECTION

When a patient who has been taking DILAUDID INJECTION regularly and may be physically dependent no longer requires therapy with DILAUDID INJECTION, taper the dose gradually, by 25% to 50% every 2 to 4 days, while monitoring carefully for signs and symptoms of withdrawal. If the patient develops these signs or symptoms, raise the dose to the previous level and taper more slowly, either by increasing the interval between decreases, decreasing the amount of change in dose, or both. Do not abruptly discontinue DILAUDID INJECTION in a physically-dependent patient [see Warnings and Precautions (5.12), Drug Abuse and Dependence (9.3)].

3 DOSAGE FORMS AND STRENGTHS

DILAUDID INJECTION:

Each single-dose prefilled syringe contains 0.2 mg/mL, 0.5 mg/0.5 mL, 1 mg/mL or 2 mg/mL of hydromorphone hydrochloride in a sterile, aqueous solution.

4 CONTRAINDICATIONS

DILAUDID INJECTION is contraindicated in patients with:

- Significant respiratory depression [see Warnings and Precautions (5.2)]
- Acute or severe bronchial asthma in an unmonitored setting or in the absence of resuscitative equipment [see Warnings and Precautions (5.6)]
- Known or suspected gastrointestinal obstruction, including paralytic ileus [see Warnings and Precautions (5.10)]
- Hypersensitivity to hydromorphone, hydromorphone salts, any other components of the product, or sulfite containing medications (e.g., anaphylaxis) [see Warnings and Precautions (5.14)]

5 WARNINGS AND PRECAUTIONS

5.1 Addiction, Abuse, and Misuse

DILAUDID INJECTION contains hydromorphone, a Schedule II controlled substance. As an opioid, DILAUDID INJECTION exposes users to the risks of addiction, abuse, and misuse [see Drug Abuse and Dependence (9)].

Although the risk of addiction in any individual is unknown, it can occur in patients appropriately prescribed DILAUDID INJECTION. Addiction can occur at recommended dosages and if the drug is misused or abused.

Assess each patient's risk for opioid addiction, abuse, or misuse prior to prescribing DILAUDID INJECTION and monitor all patients receiving DILAUDID INJECTION for the development of these behaviors and conditions. Risks are increased in patients with a personal or family history of substance abuse (including drug or alcohol abuse or addiction) or mental illness (e.g., major depression). The potential for these risks should not, however, prevent the proper management of pain in any given patient. Patients at increased risk may be prescribed opioids such as DILAUDID INJECTION but use in such patients necessitates intensive counseling about the risks and proper use of DILAUDID INJECTION along with intensive monitoring for signs of addiction, abuse, and misuse.

Opioids are sought for nonmedical use and are subject to diversion from legitimate prescribed use. Consider these risks when prescribing or dispensing DILAUDID INJECTION. Strategies to reduce these risks include prescribing the drug in the smallest appropriate quantity. Contact local state professional licensing board or state-controlled substances authority for information on how to prevent and detect abuse or diversion of this product.

5.2 Life-Threatening Respiratory Depression

Serious, life-threatening, or fatal respiratory depression has been reported with the use of opioids, even when used as recommended. Respiratory depression, if not immediately recognized and treated, may lead to respiratory arrest and death. Management of respiratory depression may include close observation, supportive measures, and use of opioid antagonists, depending on the patient's clinical status [see Overdosage (10)]. Carbon dioxide (CO2) retention from opioid-induced respiratory depression can exacerbate the sedating effects of opioids.

While serious, life-threatening, or fatal respiratory depression can occur at any time during the use of DILAUDID INJECTION, the risk is greatest during the initiation of therapy or following a dosage increase.

To reduce the risk of respiratory depression, proper dosing and titration of DILAUDID INJECTION is essential [see Dosage and Administration (2)]. Overestimating the DILAUDID INJECTION dosage when converting patients from another opioid product can result in a fatal overdose with the first dose.

Opioids can cause sleep-related breathing disorders including central sleep apnea (CSA) and sleep-related hypoxemia. Opioid use increases the risk of CSA in a dose-dependent fashion. In patients who present with CSA, consider decreasing the opioid dosage using best practices for opioid taper [see Dosage and Administration (2.6)].

5.3 Risks from Concomitant Use with Benzodiazepines or Other CNS Depressants

Profound sedation, respiratory depression, coma, and death may result from the concomitant use of DILAUDID INJECTION with benzodiazepines and/or other CNS depressants, including alcohol (e.g., non-benzodiazepine sedatives/hypnotics, anxiolytics, tranquilizers, muscle relaxants, general anesthetics, antipsychotics, other opioids). Because of these risks, reserve concomitant prescribing of these drugs for use in patients for whom alternative treatment options are inadequate.

Observational studies have demonstrated that concomitant use of opioid analgesics and benzodiazepines increases the risk of drug-related mortality compared to use of opioid analgesics alone. Because of similar pharmacological properties, it is reasonable to expect similar risk with the concomitant use of other CNS depressant drugs with opioid analgesics [see Drug Interactions (7)].

If the decision is made to prescribe a benzodiazepine or other CNS depressant concomitantly with an opioid analgesic, prescribe the lowest effective dosages and minimum durations of concomitant use. In patients already receiving an opioid analgesic, prescribe a lower initial dose of the benzodiazepine or other CNS depressant than indicated in the absence of an opioid, and titrate based on clinical response. If an opioid analgesic is initiated in a patient already taking a benzodiazepine or other CNS depressant, prescribe a lower initial dose of the opioid analgesic, and titrate based on clinical response. Monitor patients closely for signs and symptoms of respiratory depression and sedation.

5.4 Neonatal Opioid Withdrawal Syndrome

Use of Hydromorphone Hydrochloride Injection for an extended period of time during pregnancy can result in withdrawal in the neonate. Neonatal opioid withdrawal syndrome, unlike opioid withdrawal syndrome in adults, may be life-threatening if not recognized and treated, and requires management according to protocols developed by neonatology experts. Observe newborns for signs of neonatal opioid withdrawal syndrome and manage accordingly. Advise pregnant women using opioids for an extended period of time of the risk of neonatal opioid withdrawal syndrome and ensure that management by neonatology experts will be available at delivery [see Use in Specific Populations (8.1)].

5.5 Opioid-Induced Hyperalgesia and Allodynia

Opioid-Induced Hyperalgesia (OIH) occurs when an opioid analgesic paradoxically causes an increase in pain, or an increase in sensitivity to pain. This condition differs from tolerance, which is the need for increasing doses of opioids to maintain a defined effect [see Dependence (9.3)]. Symptoms of OIH include (but may not be limited to) increased levels of pain upon opioid dosage increase, decreased levels of pain upon opioid dosage decrease, or pain from ordinarily non-painful stimuli (allodynia). These symptoms may suggest OIH only if there is no evidence of underlying disease progression, opioid tolerance, opioid withdrawal, or addictive behavior.

Cases of OIH have been reported, both with short-term and longer-term use of opioid analgesics. Though the mechanism of OIH is not fully understood, multiple biochemical pathways have been implicated. Medical literature suggests a strong biologic plausibility between opioid analgesics and OIH and allodynia. If a patient is suspected to be experiencing OIH, carefully consider appropriately decreasing the dose of the current opioid analgesic or opioid rotation (safely switching the patient to a different opioid moiety) [see Dosage and Administration (2.6), Warnings and Precautions (5.12)].

5.6 Life-Threatening Respiratory Depression in Patients with Chronic Pulmonary Disease or in Elderly, Cachectic, or Debilitated Patients

The use of DILAUDID INJECTION in patients with acute or severe bronchial asthma in an unmonitored setting or in the absence of resuscitative equipment is contraindicated.

Patients with Chronic Pulmonary Disease: DILAUDID INJECTION treated patients with significant chronic obstructive pulmonary disease or cor pulmonale, and those with a substantially decreased respiratory reserve, hypoxia, hypercapnia, or pre-existing respiratory depression are at increased risk of decreased respiratory drive including apnea, even at recommended dosages of DILAUDID INJECTION [see Warnings and Precautions (5.2)].

Elderly, Cachectic, or Debilitated Patients: Life-threatening respiratory depression is more likely to occur in elderly, cachectic, or debilitated patients because they may have altered pharmacokinetics or altered clearance compared to younger, healthier patients [see Warnings and Precautions (5.2)].

Monitor such patients closely, particularly when initiating and titrating DILAUDID INJECTION and when DILAUDID INJECTION is given concomitantly with other drugs that depress respiration [see Warnings and Precautions (5.2, 5.3), Drug Interactions (7)]. Alternatively, consider the use of non-opioid analgesics in these patients.

5.7 Adrenal Insufficiency

Cases of adrenal insufficiency have been reported with opioid use, more often following greater than one month of use. Presentation of adrenal insufficiency may include non-specific symptoms and signs including nausea, vomiting, anorexia, fatigue, weakness, dizziness, and low blood pressure. If adrenal insufficiency is suspected, confirm the diagnosis with diagnostic testing as soon as possible. If adrenal insufficiency is diagnosed, treat with physiologic replacement doses of corticosteroids. Wean the patient off of the opioid to allow adrenal function to recover and continue corticosteroid treatment until adrenal function recovers. Other opioids may be tried as some cases reported use of a different opioid without recurrence of adrenal insufficiency. The information available does not identify any particular opioids as being more likely to be associated with adrenal insufficiency.

5.8 Severe Hypotension

DILAUDID INJECTION may cause severe hypotension including orthostatic hypotension and syncope in ambulatory patients. There is increased risk in patients whose ability to maintain blood pressure has already been compromised by a reduced blood volume or concurrent administration of certain CNS depressant drugs (e.g., phenothiazines or general anesthetics) [see Drug Interactions (7)]. Monitor these patients for signs of hypotension after initiating or titrating the dosage of DILAUDID INJECTION. In patients with circulatory shock, DILAUDID INJECTION may cause vasodilation that can further reduce cardiac output and blood pressure. Avoid the use of DILAUDID INJECTION in patients with circulatory shock.

5.9 Risks of Use in Patients with Increased Intracranial Pressure, Brain Tumors, Head Injury, or Impaired Consciousness

In patients who may be susceptible to the intracranial effects of CO2 retention (e.g., those with evidence of increased intracranial pressure or brain tumors), DILAUDID INJECTION may reduce respiratory drive, and the resultant CO2 retention can further increase intracranial pressure. Monitor such patients for signs of sedation and respiratory depression, particularly when initiating therapy with DILAUDID INJECTION.

Opioids may also obscure the clinical course in a patient with a head injury. Avoid the use of DILAUDID INJECTION in patients with impaired consciousness or coma.

5.10 Risks of Use in Patients with Gastrointestinal Conditions

DILAUDID INJECTION is contraindicated in patients with known or suspected gastrointestinal obstruction, including paralytic ileus.

The hydromorphone in DILAUDID INJECTION may cause spasm of the sphincter of Oddi. Opioids may cause increases in serum amylase. Monitor patients with biliary tract disease, including acute pancreatitis, for worsening symptoms.

5.11 Increased Risk of Seizures in Patients with Seizure Disorders

The hydromorphone in DILAUDID INJECTION may increase the frequency of seizures in patients with seizure disorders and may increase the risk of seizures occurring in other clinical settings associated with seizures. Monitor patients with a history of seizure disorders for worsened seizure control during DILAUDID INJECTION therapy.

5.12 Withdrawal

Avoid the use of mixed agonist/antagonist (e.g., pentazocine, nalbuphine, and butorphanol) or partial agonist (e.g., buprenorphine) analgesics in patients who are receiving a full opioid agonist analgesic, including DILAUDID INJECTION. In these patients, mixed agonist/antagonist and partial agonist analgesics may reduce the analgesic effect and/or precipitate withdrawal symptoms [see Drug Interactions (7)].

When discontinuing DILAUDID INJECTION in a physically-dependent patient, gradually taper the dosage [see Dosage and Administration (2.6)]. Do not abruptly discontinue DILAUDID INJECTION in these patients [see Drug Abuse and Dependence (9.3)].

5.13 Risks of Driving and Operating Machinery

DILAUDID INJECTION may impair the mental or physical abilities needed to perform potentially hazardous activities such as driving a car or operating machinery. Warn patients not to drive or operate dangerous machinery unless they are tolerant to the effects of DILAUDID INJECTION and know how they will react to the medication.

5.14 Sulfites

DILAUDID INJECTION contains sodium metabisulfite, a sulfite that may cause allergic-type reactions including anaphylactic symptoms and life- threatening or less severe asthmatic episodes in certain susceptible people. The overall prevalence of sulfite sensitivity in the general population is unknown and probably low. Sulfite sensitivity is seen more frequently in asthmatic than in nonasthmatic people.

5.15 Increased Risk of Hypotension and Respiratory Depression with Rapid Intravenous Administration

DILAUDID INJECTION may be given intravenously, but the injection should be given very slowly. Rapid intravenous injection of opioid analgesics increases the possibility of side effects such as hypotension and respiratory depression [see Dosage and Administration (2)].

6 ADVERSE REACTIONS

The following serious adverse reactions are described, or described in greater detail, in other sections:

- Addiction, Abuse, and Misuse [see Warnings and Precautions (5.1)]
- Life-Threatening Respiratory Depression [see Warnings and Precautions (5.2)]
- Interactions with Benzodiazepines and Other CNS Depressants [see Warnings and Precautions (5.3)]
- Neonatal Opioid Withdrawal Syndrome [see Warnings and Precautions (5.4)]
- Opioid-Induced Hyperalgesia and Allodynia [see Warnings and Precautions (5.5)]
- Adrenal Insufficiency [see Warnings and Precautions (5.7)]
- Severe Hypotension [see Warnings and Precautions (5.8)]
- Gastrointestinal Adverse Reactions [see Warnings and Precautions (5.10)]
- Seizures [see Warnings and Precautions (5.11)]
- Withdrawal [see Warnings and Precautions (5.12)]

The following adverse reactions associated with the use of hydromorphone were identified in clinical studies or postmarketing reports. Because some of these reactions were reported voluntarily from a population of uncertain size, it is not always possible to reliably estimate their frequency or establish a causal relationship to drug exposure.

Serious adverse reactions associated with DILAUDID INJECTION include respiratory depression and apnea and, to a lesser degree, circulatory depression, respiratory arrest, shock, and cardiac arrest.

The most common adverse effects are lightheadedness, dizziness, sedation, nausea, vomiting, sweating, flushing, dysphoria, euphoria, dry mouth, and pruritus. These effects seem to be more prominent in ambulatory patients and in those not experiencing severe pain.

Less Frequently Observed Adverse Reactions

Cardiac disorders: tachycardia, bradycardia, palpitations

Eye disorders: vision blurred, diplopia, miosis, visual impairment

Gastrointestinal disorders: constipation, ileus, diarrhea, abdominal pain

General disorders and administration site conditions: weakness, feeling abnormal, chills, injection site urticaria, fatigue, injection site reactions, peripheral edema

Hepatobiliary disorders: biliary colic

Immune system disorders: anaphylactic reactions, hypersensitivity reactions

Investigations: hepatic enzymes increased

Metabolism and nutrition disorders: decreased appetite

Musculoskeletal and connective tissue disorders: muscle rigidity

Nervous system disorders: headache, tremor, paraesthesia, nystagmus, increased intracranial pressure, syncope, taste alteration, involuntary muscle contractions, presyncope, convulsion, drowsiness, dyskinesia, hyperalgesia, lethargy, myoclonus, somnolence

Psychiatric disorders: agitation, mood altered, nervousness, anxiety, depression, hallucination, disorientation, insomnia, abnormal dreams

Renal and urinary disorders: urinary retention, urinary hesitation, antidiuretic effects

Reproductive system and breast disorders: erectile dysfunction

Respiratory, thoracic, and mediastinal disorders: bronchospasm, laryngospasm, dyspnea, oropharyngeal swelling

Skin and subcutaneous tissue disorders: injection site pain, urticaria, rash, hyperhidrosis

Vascular disorders: flushing, hypotension, hypertension

Serotonin syndrome: Cases of serotonin syndrome, a potentially life-threatening condition, have been reported during concomitant use of opioids with serotonergic drugs.

Adrenal insufficiency: Cases of adrenal insufficiency have been reported with opioid use, more often following greater than one month of use. Anaphylaxis: Anaphylaxis has been reported with ingredients contained in DILAUDID INJECTION.

Androgen deficiency: Cases of androgen deficiency have occurred with use of opioids for an extended period of time [see Clinical Pharmacology (12.2)].

Hyperalgesia and Allodynia: Cases of hyperalgesia and allodynia have been reported with opioid therapy of any duration [see Warnings and Precautions (5.5)]

Hypoglycemia: Cases of hypoglycemia have been reported in patients taking opioids. Most reports were in patients with at least one predisposing risk factor (e.g., diabetes).

7 DRUG INTERACTIONS

Table 1 includes clinically significant drug interactions with DILAUDID INJECTION.

Table 1. Clinically Significant Drug Interactions with DILAUDID INJECTION
Benzodiazepines and other Central Nervous System Depressants (CNS)
Clinical Impact: | Due to additive pharmacologic effect, the concomitant use of benzodiazepines and other CNS depressants, including alcohol, can increase the risk of hypotension, respiratory depression, profound sedation, coma, and death. [see Warnings and Precautions (5.3)]
Intervention: | Reserve concomitant prescribing of these drugs for use in patients for whom alternative treatment options are inadequate. Limit dosages and durations to the minimum required. Monitor patients closely for signs of respiratory depression and sedation [see Warnings and Precautions (5.3)].
Examples: | Benzodiazepines and other sedatives/hypnotics, anxiolytics, tranquilizers, muscle relaxants, general anesthetics, antipsychotics, other opioids, alcohol.
Serotonergic Drugs
Clinical Impact: | The concomitant use of opioids with other drugs that affect the serotonergic neurotransmitter system has resulted in serotonin syndrome.
Intervention: | If concomitant use is warranted, carefully observe the patient, particularly during treatment initiation and dose adjustment. Discontinue DILAUDID INJECTION if serotonin syndrome is suspected.
Examples: | Selective serotonin reuptake inhibitors (SSRIs), serotonin and norepinephrine reuptake inhibitors (SNRIs), tricyclic antidepressants (TCAs), triptans, 5-HT3 receptor antagonists, drugs that effect the serotonin neurotransmitter system (e.g., mirtazapine, trazodone, tramadol), certain muscle relaxants (i.e., cyclobenzaprine, metaxalone), monoamine oxidase (MAO) inhibitors (those intended to treat psychiatric disorders and also others, such as linezolid and intravenous methylene blue).
Monoamine Oxidase Inhibitors (MAOIs)
Clinical Impact: | MAOI interactions with opioids may manifest as serotonin syndrome or opioid toxicity (e.g., respiratory depression, coma) [see Warnings and Precautions (5.2)].; If urgent use of an opioid is necessary, use test doses and frequent titration of small doses to treat pain while closely monitoring blood pressure and signs and symptoms of CNS and respiratory depression.
Intervention: | The use of DILAUDID INJECTION is not recommended for patients taking MAOIs or within 14 days of stopping such treatment. If urgent use of an opioid is necessary, use test doses and frequent titration of small doses while closely monitoring blood pressure and signs and symptoms of CNS and respiratory depression.
Examples: | phenelzine, tranylcypromine, linezolid
Mixed Agonist/Antagonist and Partial Agonist Opioid Analgesics
Clinical Impact: | May reduce the analgesic effect of DILAUDID INJECTION and/or precipitate withdrawal syndrome.
Intervention: | Avoid concomitant use.
Examples: | butorphanol, nalbuphine, pentazocine, buprenorphine
Muscle Relaxants
Clinical Impact: | Hydromorphone may enhance the neuromuscular blocking action of skeletal muscle relaxants and produce an increased degree of respiratory depression.
Intervention: | Monitor patients for signs of respiratory depression that may be greater than otherwise expected and decrease the dosage of DILAUDID INJECTION and/or the muscle relaxant as necessary.
Diuretics
Clinical Impact: | Opioids can reduce the efficacy of diuretics by inducing the release of antidiuretic hormone.
Intervention: | Monitor patients for signs of diminished diuresis and/or effects on blood pressure and increase the dosage of the diuretic as needed.
Anticholinergic Drugs
Clinical Impact: | The concomitant use of anticholinergic drugs may increase risk of urinary retention and/or severe constipation, which may lead to paralytic ileus.
Intervention: | Monitor patients for signs of urinary retention or reduced gastric motility when DILAUDID INJECTION is used concomitantly with anticholinergic drugs.

8 USE IN SPECIFIC POPULATIONS

8.1 Pregnancy

Risk Summary

Use of opioid analgesics for an extended period of time during pregnancy may cause neonatal opioid withdrawal syndrome [see Warnings and Precautions (5.4)]. There are no available data with DILAUDID INJECTION in pregnant women to inform a drug-associated risk for major birth defects and miscarriage or adverse maternal outcomes. There are adverse outcomes reported with fetal exposure to opioid analgesics (see Clinical Considerations).

In animal reproduction studies, reduced postnatal survival of pups, and decreased body weight were noted following oral treatment of pregnant rats with hydromorphone during gestation and through lactation at doses 0.8 times the human daily dose of 24 mg/day (HDD), respectively. In published studies, neural tube defects were noted following subcutaneous injection of hydromorphone to pregnant hamsters at doses 6.4 times the HDD and soft tissue and skeletal abnormalities were noted following subcutaneous continuous infusion of 3 times the HDD to pregnant mice. No malformations were noted at 4 or 40.5 times the HDD in pregnant rats or rabbits, respectively [see Data]. Based on animal data, advise pregnant women of the potential risk to a fetus.

The background risk of major birth defects and miscarriage for the indicated population is unknown. All pregnancies have a background risk of birth defect, loss, or other adverse outcomes. In the U.S. general population, the estimated background risk of major birth defects and miscarriage in clinically recognized pregnancies is 2 to 4% and 15 to 20%, respectively.

Clinical Considerations

Fetal/Neonatal Adverse Reactions

Use of opioid analgesics for an extended period of time during pregnancy for medical or nonmedical purposes can result in physical dependence in the neonate and neonatal opioid withdrawal syndrome shortly after birth.

Neonatal opioid withdrawal syndrome presents as irritability, hyperactivity and abnormal sleep pattern, high pitched cry, tremor, vomiting, diarrhea, and failure to gain weight. The onset, duration, and severity of neonatal opioid withdrawal syndrome vary based on the specific opioid used, duration of use, timing and amount of last maternal use, and rate of elimination of the drug by the newborn. Observe newborns for symptoms of neonatal opioid withdrawal syndrome and manage accordingly [see Warnings and Precautions (5.4)].

Labor or Delivery

Opioids cross the placenta and may produce respiratory depression and psycho-physiologic effects in neonates. An opioid antagonist, such as naloxone, must be available for reversal of opioid-induced respiratory depression in the neonate. DILAUDID INJECTION is not recommended for use in pregnant women during or immediately prior to labor, when other analgesic techniques are more appropriate. Opioid analgesics, including DILAUDID INJECTION, can prolong labor through actions which temporarily reduce the strength, duration, and frequency of uterine contractions. However, this effect is not consistent and may be offset by an increased rate of cervical dilation, which tends to shorten labor.

Monitor neonates exposed to opioid analgesics during labor for signs of excess sedation and respiratory depression.

Data

Animal Data

Pregnant rats were treated with hydromorphone hydrochloride from Gestation Day 6 to 17 via oral gavage doses of 1, 5, or 10 mg/kg/day (0.4, 2, or 4 times the HDD of 24 mg based on body surface area, respectively). Maternal toxicity was noted in all treatment groups (reduced food consumption and body weights in the two highest dose groups). There was no evidence of malformations or embryotoxicity reported.

Pregnant rabbits were treated with hydromorphone hydrochloride from Gestation Day 7 to 19 via oral gavage doses of 10, 25, or 50 mg/kg/day (8.1, 20.3, or 40.5 times the HDD of 24 mg based on body surface area, respectively). Maternal toxicity was noted in the two highest dose groups (reduced food consumption and body weights). There was no evidence of malformations or embryotoxicity reported.

In a published study, neural tube defects (exencephaly and cranioschisis) were noted following subcutaneous administration of hydromorphone hydrochloride (19 to 258 mg/kg) on Gestation Day 8 to pregnant hamsters (6.4 to 87.2 times the HDD of 24 mg/day based on body surface area). The findings cannot be clearly attributed to maternal toxicity. No neural tube defects were noted at 14 mg/kg (4.7 times the human daily dose of 24 mg/day).

In a published study, CF-1 mice were treated subcutaneously with continuous infusion of 7.5, 15, or 30 mg/kg/day hydromorphone hydrochloride (1.5, 3, or 6.1 times the human daily dose of 24 mg based on body surface area) via implanted osmotic pumps during organogenesis (Gestation Days 7 to 10). Soft tissue malformations (cryptorchidism, cleft palate, malformed ventricles and retina), and skeletal variations (split supraoccipital, checkerboard and split sternebrae, delayed ossification of the paws and ectopic ossification sites) were observed at doses 3 times the human dose of 24 mg/day based on body surface area. The findings cannot be clearly attributed to maternal toxicity.

Increased pup mortality and decreased pup body weights were noted at 0.8 and 2 times the human daily dose of 24 mg in a study in which pregnant rats were treated with hydromorphone hydrochloride from Gestation Day 7 to Lactation Day 20 via oral gavage doses of 0, 0.5, 2, or 5 mg/kg/day (0.2, 0.8, or 2 times the HDD of 24 mg based on body surface area, respectively). Maternal toxicity (decreased food consumption and body weight gain) was also noted at the two highest doses tested.

8.2 Lactation

Risk Summary

Low levels of opioid analgesics have been detected in human milk. The developmental and health benefits of breastfeeding should be considered along with the mother's clinical need for DILAUDID INJECTION and any potential adverse effects on the breastfed infant from DILAUDID INJECTION or from the underlying maternal condition.

Clinical Considerations

Monitor infants exposed to DILAUDID INJECTION through breast milk for excess sedation and respiratory depression. Withdrawal symptoms can occur in breastfed infants when maternal administration of hydromorphone is stopped, or when breast-feeding is stopped.

8.3 Females and Males of Reproductive Potential

Infertility

Use of opioids for an extended period of time may cause reduced fertility in females and males of reproductive potential. It is not known whether these effects on fertility are reversible [see Adverse Reactions (6), Clinical Pharmacology (12.2), Nonclinical Toxicology (13.1)].

8.4 Pediatric Use

The safety and effectiveness of DILAUDID INJECTION in pediatric patients has not been established.

8.5 Geriatric Use

Elderly patients (aged 65 years or older) may have increased sensitivity to hydromorphone. In general, use caution when selecting a dosage for an elderly patient, usually starting at the low end of the dosing range, reflecting the greater frequency of decreased hepatic, renal, or cardiac function and of concomitant disease or other drug therapy.

Respiratory depression is the chief risk for elderly patients treated with opioids, and has occurred after large initial doses were administered to patients who were not opioid-tolerant or when opioids were co-administered with other agents that depress respiration. Titrate the dosage of DILAUDID INJECTION slowly in geriatric patients and monitor closely for signs of central nervous system and respiratory depression [see Warnings and Precautions (5.6)].

Hydromorphone is known to be substantially excreted by the kidney, and the risk of adverse reactions to this drug may be greater in patients with impaired renal function. Because elderly patients are more likely to have decreased renal function, care should be taken in dose selection, and it may be useful to monitor renal function.

8.6 Hepatic Impairment

The pharmacokinetics of hydromorphone are affected by hepatic impairment. Due to increased exposure of hydromorphone, patients with moderate hepatic impairment should be started at one-fourth to one-half the recommended starting dose depending on the degree of hepatic dysfunction and closely monitored during dose titration. The pharmacokinetics of hydromorphone in patients with severe hepatic impairment has not been studied. A further increase in Cmax and AUC of hydromorphone in this group is expected and should be taken into consideration when selecting a starting dose [see Clinical Pharmacology (12.3)].

8.7 Renal Impairment

The pharmacokinetics of hydromorphone are affected by renal impairment. Start patients with renal impairment on one-fourth to one-half the usual starting dose depending on the degree of impairment. Patients with renal impairment should be closely monitored during dose titration [see Clinical Pharmacology (12.3)].

9 DRUG ABUSE AND DEPENDENCE

9.1 Controlled Substance

DILAUDID INJECTION contains hydromorphone, which is a Schedule II controlled substance.

9.2 Abuse

DILAUDID INJECTION contains hydromorphone, a substance with high potential for misuse and abuse, which can lead to the development of substance use disorder, including addiction [see Warnings and Precautions (5.1)].

Misuse is the intentional use, for therapeutic purposes, of a drug by an individual in a way other than prescribed by a healthcare provider or for whom it was not prescribed.

Abuse is the intentional, non-therapeutic use of a drug, even once, for its desirable psychological or physiological effects.

Drug addiction is a cluster of behavioral, cognitive, and physiological phenomena that may include a strong desire to take the drug, difficulties in controlling drug use (e.g., continuing drug use despite harmful consequences, giving a higher priority to drug use than other activities and obligations), and possible tolerance or physical dependence.

Misuse and abuse of DILAUDID INJECTION increases risk of overdose, which may lead to central nervous system and respiratory depression, hypotension, seizures, and death. The risk is increased with concurrent abuse of DILAUDID INJECTION with alcohol and/or other CNS depressants. Abuse of and addiction to opioids in some individuals may not be accompanied by concurrent tolerance and symptoms of physical dependence. In addition, abuse of opioids can occur in the absence of addiction.

All patients treated with opioids require careful and frequent reevaluation for signs of misuse, abuse, and addiction, because use of opioid analgesic products carries the risk of addiction even under appropriate medical use. Patients at high risk of DILAUDID INJECTION abuse include those with a history of prolonged use of any opioid, including products containing hydromorphone, those with a history of drug or alcohol abuse, or those who use DILAUDID INJECTION in combination with other abused drugs.

“Drug-seeking” behavior is very common in persons with substance use disorders. Drug-seeking tactics include emergency calls or visits near the end of office hours, refusal to undergo appropriate examination, testing, or referral, repeated “loss” of prescriptions, tampering with prescriptions, and reluctance to provide prior medical records or contact information for other treating healthcare provider(s). “Doctor shopping” (visiting multiple prescribers to obtain additional prescriptions) is common among people who abuse drugs and people with substance use disorder. Preoccupation with achieving adequate pain relief can be appropriate behavior in a patient with inadequate pain control.

DILAUDID INJECTION, like other opioids, can be diverted for nonmedical use into illicit channels of distribution. Careful record-keeping of prescribing information, including quantity, frequency, and renewal requests, as required by state and federal law, is strongly advised.

Proper assessment of the patient, proper prescribing practices, periodic reevaluation of therapy, and proper dispensing and storage are appropriate measures that help to limit abuse of opioid drugs.

Risks Specific to Abuse of DILAUDID INJECTION

Abuse of DILAUDID INJECTION poses a risk of overdose and death. The risk is increased with concurrent use of DILAUDID INJECTION with alcohol and/or other CNS depressants.

Parenteral drug abuse is commonly associated with transmission of infectious diseases such as hepatitis and HIV.

9.3 Dependence

Both tolerance and physical dependence can develop during use of opioid therapy.

Tolerance is a physiological state characterized by a reduced response to a drug after repeated administration (i.e., a higher dose of a drug is required to produce the same effect that was once obtained at a lower dose).

Physical dependence is a state that develops as a result of a physiological adaptation in response to repeated drug use, manifested by withdrawal signs and symptoms after abrupt discontinuation or a significant dose reduction of a drug.

Withdrawal may be precipitated through the administration of drugs with opioid antagonist activity (e.g., naloxone), mixed agonist/antagonist analgesics (e.g., pentazocine, butorphanol, nalbuphine), or partial agonists (e.g., buprenorphine). Physical dependence may not occur to a clinically significant degree until after several days to weeks of continued use.

DILAUDID INJECTION should not be abruptly discontinued in a physically-dependent patient [see Dosage and Administration (2.6)]. If DILAUDID INJECTION is abruptly discontinued in a physically-dependent patient, a withdrawal syndrome may occur, typically characterized by restlessness, lacrimation, rhinorrhea, perspiration, chills, myalgia, and mydriasis. Other signs and symptoms also may develop, including irritability, anxiety, backache, joint pain, weakness, abdominal cramps, insomnia, nausea, anorexia, vomiting, diarrhea, or increased blood pressure, respiratory rate, or heart rate.

Infants born to mothers physically dependent on opioids will also be physically dependent and may exhibit respiratory difficulties and withdrawal signs [see Use in Specific Populations (8.1)].

10 OVERDOSAGE

Clinical Presentation

Acute overdose with hydromorphone can be manifested by respiratory depression, somnolence progressing to stupor or coma, skeletal muscle flaccidity, cold and clammy skin, constricted pupils, and, in some cases, pulmonary edema, bradycardia, hypotension, hypoglycemia, partial or complete airway obstruction, atypical snoring, and death. Marked mydriasis, rather than miosis, may be seen with hypoxia in overdose situations [see Clinical Pharmacology (12.2)].

Treatment of Overdose

In case of overdose, priorities are the reestablishment of a patent airway and protected airway and institution of assisted or controlled ventilation, if needed. Employ other supportive measures (including oxygen and vasopressors) in the management of circulatory shock and pulmonary edema as indicated. Cardiac arrest or arrhythmias will require advanced life-support measures.

Opioid antagonists, such as naloxone are specific antidotes to respiratory depression resulting from opioid overdose. For clinically significant respiratory or circulatory depression secondary to hydromorphone overdose, administer an opioid antagonist. Opioid antagonists should not be administered in the absence of clinically significant respiratory or circulatory depression secondary to hydromorphone overdose.

Because the duration of opioid reversal is expected to be less than the duration of hydromorphone in DILAUDID INJECTION, carefully monitor the patient until spontaneous respiration is reliably reestablished. If the response to an opioid antagonist is suboptimal or only brief in nature, administer additional antagonist as directed by the product's prescribing information.

In an individual physically dependent on opioids, administration of the recommended usual dosage of the antagonist will precipitate an acute withdrawal syndrome. The severity of the withdrawal symptoms experienced will depend on the degree of physical dependence and the dose of the antagonist administered. If a decision is made to treat serious respiratory depression in the physically dependent patient, administration of the antagonist should be initiated with care and by titration with smaller than usual doses of the antagonist.

11 DESCRIPTION

DILAUDID (hydromorphone hydrochloride), a hydrogenated ketone of morphine, is an opioid agonist.

DILAUDID INJECTION is available as a sterile, aqueous solution in clear and colorless single-dose prefilled syringes for slow intravenous, subcutaneous, or intramuscular administration. Each 1 mL of solution contains 0.2 mg, 1 mg or 2 mg of hydromorphone hydrochloride.

The chemical name of DILAUDID is 4,5α-epoxy-3-hydroxy-17-methylmorphinan-6-one hydrochloride. The molecular weight is 321.80. Its molecular formula is C17H19NO3·HCl, and it has the following chemical structure:

Hydromorphone hydrochloride is a white or almost white crystalline powder that is freely soluble in water, very slightly soluble in ethanol (96%), and practically insoluble in methylene chloride.

The inactive ingredients in DILAUDID (hydromorphone hydrochloride) include: 0.2% sodium citrate and 0.2% citric acid added as a buffer to maintain a pH between 3.5 and 5.5.

12 CLINICAL PHARMACOLOGY

12.1 Mechanism of Action

Hydromorphone is a full opioid agonist and is relatively selective for the mu-opioid receptor, although it can bind to other opioid receptors at higher doses. The principal therapeutic action of hydromorphone is analgesia. Like all full opioid agonists, there is no ceiling effect for analgesia with morphine. Clinically, dosage is titrated to provide adequate analgesia and may be limited by adverse reactions, including respiratory and CNS depression.

The precise mechanism of the analgesic action is unknown. However, specific CNS opioid receptors for endogenous compounds with opioid-like activity have been identified throughout the brain and spinal cord and are thought to play a role in the analgesic effects of this drug.

12.2 Pharmacodynamics

Effects on the Central Nervous System

Hydromorphone produces respiratory depression by direct effect on brain stem respiratory centers. The respiratory depression involves a reduction in the responsiveness of the brain stem respiratory centers to both increases in carbon dioxide tension and electrical stimulation.

Hydromorphone causes miosis, even in total darkness. Pinpoint pupils are a sign of opioid overdose but are not pathognomonic (e.g., pontine lesions of hemorrhagic or ischemic origin may produce similar findings). Marked mydriasis rather than miosis may be seen due to hypoxia in overdose situations.

Effects on the Gastrointestinal Tract and Other Smooth Muscle

Hydromorphone causes a reduction in motility associated with an increase in smooth muscle tone in the antrum of the stomach and duodenum. Digestion of food in the small intestine is delayed and propulsive contractions are decreased. Propulsive peristaltic waves in the colon are decreased, while tone may be increased to the point of spasm, resulting in constipation. Other opioid-induced effects may include a reduction in biliary and pancreatic secretions, spasm of sphincter of Oddi, and transient elevations in serum amylase.

Effects on the Cardiovascular System

Hydromorphone produces peripheral vasodilation which may result in orthostatic hypotension or syncope, manifestations of histamine release and/or peripheral vasodilation may include pruritus, flushing, red eyes, and sweating and/or orthostatic hypotension.

Effects on the Endocrine System

Opioids inhibit the secretion of adrenocorticotropic hormone (ACTH), cortisol, and luteinizing hormone (LH) in humans [see Adverse Reactions (6)]. They also stimulate prolactin, growth hormone (GH) secretion, and pancreatic secretion of insulin and glucagon.

Use of opioids for an extended period of time may influence the hypothalamic-pituitary-gonadal axis, leading to androgen deficiency that may manifest as low libido, impotence, erectile dysfunction, amenorrhea, or infertility. The causal role of opioids in the clinical syndrome of hypogonadism is unknown because the various medical, physical, lifestyle, and psychological stressors that may influence gonadal hormone levels have not been adequately controlled for in studies conducted to date [see Adverse Reactions (6)].

Effects on the Immune System

Opioids have been shown to have a variety of effects on components of the immune system in in vitro and animal models. The clinical significance of these findings is unknown. Overall, the effects of opioids appear to be modestly immunosuppressive.

Concentration–Efficacy Relationships

The minimum effective analgesic concentration will vary widely among patients, especially among patients who have been previously treated with opioid agonists. The minimum effective analgesic concentration of hydromorphone for any individual patient may increase over time due to an increase in pain, the development of a new pain syndrome, and/or the development of analgesic tolerance [see Dosage and Administration (2.1, 2.2)].

Concentration–Adverse Reaction Relationships

There is a relationship between increasing hydromorphone plasma concentration and increasing frequency of dose-related opioid adverse reactions such as nausea, vomiting, CNS effects, and respiratory depression. In opioid-tolerant patients, the situation may be altered by the development of tolerance to opioid-related adverse reactions [see Dosage and Administration (2.1, 2.2)].

12.3 Pharmacokinetics

Distribution

At therapeutic plasma levels, hydromorphone is approximately 8-19% bound to plasma proteins. After an intravenous bolus dose, the steady state of volume of distribution [mean (%CV)] is 302.9 (32%) liters.

Elimination

The systemic clearance is approximately 1.96 (20%) liters/minute. The terminal elimination half-life of hydromorphone after an intravenous dose is about 2.3 hours.

Metabolism

Hydromorphone is extensively metabolized via glucuronidation in the liver, with greater than 95% of the dose metabolized to hydromorphone-3- glucuronide along with minor amounts of 6-hydroxy reduction metabolites.

Excretion

Only a small amount of the hydromorphone dose is excreted unchanged in the urine. Most of the dose is excreted as hydromorphone-3-glucuronide along with minor amounts of 6-hydroxy reduction metabolites.

Special Populations

Hepatic Impairment

After oral administration of hydromorphone at a single 4 mg dose (2 mg hydromorphone immediate-release tablets), mean exposure to hydromorphone (Cmax and AUC∞) is increased 4-fold in patients with moderate (Child-Pugh Group B) hepatic impairment compared with subjects with normal hepatic function. Patients with moderate hepatic impairment should be started at one-fourth to one-half the recommended starting dose and closely monitored during dose titration. The pharmacokinetics of hydromorphone in patients with severe hepatic impairment has not been studied. A further increase in Cmax and AUC of hydromorphone in this group is expected and should be taken into consideration when selecting a starting dose [see Use in Specific Populations (8.6)].

Renal Impairment

The pharmacokinetics of hydromorphone following an oral administration of hydromorphone at a single 4 mg dose (2 mg hydromorphone immediate-release tablets) are affected by renal impairment. Mean exposure to hydromorphone (Cmax and AUC0-∞) is increased by 2-fold in patients with moderate (CLcr = 40 - 60 mL/min) renal impairment and increased by 4-fold in patients with severe (CLcr< 30 mL/min) renal impairment compared with normal subjects (CLcr> 80 mL/min). In addition, in patients with severe renal impairment, hydromorphone appeared to be more slowly eliminated with a longer terminal elimination half-life (40 hr) compared to patients with normal renal function (15 hr). Start patients with renal impairment on one-fourth to one-half the usual starting dose depending on the degree of impairment. Patients with renal impairment should be closely monitored during dose titration [see Use in Specific Populations (8.7)].

Geriatric Population

In the geriatric population, age has no effect on the pharmacokinetics of hydromorphone.

Sex

Sex has little effect on the pharmacokinetics of hydromorphone. Females appear to have a higher Cmax (25%) than males with comparable AUC0- 24 values. The difference observed in Cmax may not be clinically relevant.

13 NONCLINICAL TOXICOLOGY

13.1 Carcinogenesis, Mutagenesis, Impairment of Fertility

Carcinogenesis

Long term studies in animals to evaluate the carcinogenic potential of hydromorphone have not been conducted.

Mutagenesis

Hydromorphone was positive in the mouse lymphoma assay in the presence of metabolic activation, but was negative in the mouse lymphoma assay in the absence of metabolic activation. Hydromorphone was not mutagenic in the in vitro bacterial reverse mutation assay (Ames assay). Hydromorphone was not clastogenic in either the in vitro human lymphocyte chromosome aberration assay or the in vivo mouse micronucleus assay.

Impairment of Fertility

Reduced implantation sites and viable fetuses were noted at 2.1 times the human daily dose of 32 mg/day in a study in which female rats were treated orally with 1.75, 3.5, or 7 mg/kg/day hydromorphone hydrochloride (0.5, 1.1, or 2.1 times a human daily dose of 24 mg/day (HDD) based on body surface area) beginning 14 days prior to mating through Gestation Day 7 and male rats were treated with the same hydromorphone hydrochloride doses beginning 28 days prior to and throughout mating.

16 HOW SUPPLIED/STORAGE AND HANDLING

DILAUDID INJECTION (hydromorphone hydrochloride) is supplied in clear and colorless single-dose prefilled syringes. Each single-dose prefilled syringe of sterile, aqueous solution contains 0.2 mg, 0.5 mg, 1 mg or 2 mg hydromorphone hydrochloride with 0.2% sodium citrate and 0.2% citric acid solution.

DILAUDID INJECTION contains no added preservative and is supplied as follows:

Product Code | Unit of Sale | Strength | Each
771906 | NDC 76045-009-06; Unit of 10 | 0.5 mg/0.5 mL | NDC 76045-009-96; 0.5 mL single-dose prefilled syringe
771911 | NDC 76045-009-11; Unit of 10 | 1 mg/mL | NDC 76045-009-01; 1 mL single-dose prefilled syringe
771011 | NDC 76045-010-11; Unit of 10 | 2 mg/mL | NDC 76045-010-01; 1 mL single-dose prefilled syringe
771311 | NDC 76045-121-11; Unit of 10 | 0.2 mg/mL | NDC 76045-121-01; 1 mL single-dose prefilled syringe

PROTECT FROM LIGHT.

Store at 20° to 25°C (68° to 77°F); excursions permitted to 15° to 30°C (59° to 86°F) [See USP Controlled Room Temperature].

Safety and Handling Instructions

Discard any unused portion.

Access to drugs with a potential for abuse such as DILAUDID INJECTION presents an occupational hazard for addiction in the health care industry. Routine procedures for handling controlled substances developed to protect the public may not be adequate to protect health care workers.

Implementation of more effective accounting procedures and measures to restrict access to drugs of this class (appropriate to the practice setting) may minimize the risk of self-administration by health care providers.

17 PATIENT COUNSELING INFORMATION

Addiction, Abuse, and Misuse

Inform patients that the use of DILAUDID INJECTION, even when taken as recommended, can result in addiction, abuse, and misuse, which can lead to overdose and death [see Warnings and Precautions (5.1)].

Life-Threatening Respiratory Depression

Inform patients of the risk of life-threatening respiratory depression, including information that the risk is greatest when starting DILAUDID INJECTION or when the dosage is increased, and that it can occur even at recommended dosages.

Hyperalgesia and Allodynia

Advise patients to inform their healthcare provider if they experience symptoms of hyperalgesia, including worsening pain, increased sensitivity to pain, or new pain [see Warnings and Precautions (5.5); Adverse Reactions (6.2)].

Serotonin Syndrome

Inform patients that opioids could cause a rare but potentially life-threatening condition called serotonin syndrome resulting from concomitant administration of serotonergic drugs. Warn patients of the symptoms of serotonin syndrome and to seek medical attention right away if symptoms develop after discharge from hospital. Instruct patients to inform their healthcare providers if they are taking, or plan to take serotonergic medications [see Drug Interactions (7)].

Constipation

Advise patients of the potential for severe constipation, including management instructions and when to seek medical attention [see Adverse Reactions (6)].

Healthcare professionals can telephone Fresenius Kabi USA, LLC at 1-800-551-7176 for information or to report adverse events on this product.

INSTRUCTIONS FOR USE

Figure 1: Outer Packaging (MicroVault®) and Prefilled Syringe

NOTES:

- Do not introduce any other fluid into the syringe at any time.
- Do not dilute for IV push.
- Do not re-sterilize the syringe.
- Do not use this product on a sterile field.
- This product is for single dose only.

1. Once removed from the bundle, inspect the outer packaging by verifying:
  1. Integrity of the tube and the cap.
  2. Tamper evident seal is intact (outer shrink wrap is not broken).

Do not use if the outer packaging has been damaged.

2. Hold the outer packaging with both hands. To break the tamper evident seal, hold the tube and the cap close to the seal, and twist until broken. (See Figure 2)
Figure 2
3. Remove the cap of the outer packaging by pulling it straight away from the tube to avoid dislodging the plunger rod of the syringe. (See Figure 3)
Figure 3
4. Remove the syringe from the tube.
5. Visually inspect the syringe. Parenteral drug products should be inspected visually for particulate matter and discoloration prior to administration, whenever solution and container permit.
6. Twist off the syringe tip cap. Do not remove the plastic wrap label around the luer lock collar. (See Figure 4)
Figure 4
7. Expel air bubble(s). Adjust the dose (if applicable).
8. Administer the dose ensuring that pressure is maintained on the plunger rod during the entire administration.
9. Discard the used syringe into an appropriate receptacle.

For more information concerning this drug, please call Fresenius Kabi USA, LLC at 1-800-551-7176.

To report SUSPECTED ADVERSE REACTIONS, contact Fresenius Kabi USA, LLC at 1-800-551-7176 or FDA at 1-800-FDA-1088 or www.fda.gov/medwatch.

Lake Zurich, IL 60047

www.fresenius-kabi.com/us

451594C

Dilaudid is a licensed trademark of Purdue Pharma L.P.

U.S. Patents 9,731,082 and 10,064,998

PACKAGE LABEL

PACKAGE LABEL – PRINCIPAL DISPLAY PANEL – Dilaudid 0.5 mL Single-Dose Syringe Label

For SC, IM, or slow IV use. 0.5 mL Single-Dose.

Rx only

Dilaudid® CII

HYDROmorphone HCl

Injection, USP

0.5 mg/0.5 mL

PACKAGE LABEL

PACKAGE LABEL - PRINCIPAL DISPLAY - Dilaudid 0.5 mL Single-Dose Tip Cap Label
Dilaudid® CII
HYDROmorphone HCl
Injection, USP

0.5 mg per 0.5 mL
For Subcutaneous, IM, or slow IV use.

PACKAGE LABEL

PACKAGE LABEL - PRINCIPAL DISPLAY - Dilaudid 0.5 mL Single-Dose Carton Panel
Rx only 771906 NDC 76045-009-06
Dilaudid® CII
HYDROmorphone HCl
Injection, USP

0.5 mg per 0.5 mL
For Subcutaneous, Intramuscular, or slow Intravenous use.
Do NOT dilute for IV push.
Do NOT place syringe on a Sterile Field.
10 x 0.5 mL single-dose prefilled syringes
Discard unused portion.

PACKAGE LABEL

PACKAGE LABEL – PRINCIPAL DISPLAY PANEL – Dilaudid 1 mL Single-Dose Syringe Label

For SC, IM, or slow IV use. 1 mL Single-Dose.

Rx only

Dilaudid® CII

HYDROmorphone HCl

Injection, USP

0.2 mg/mL

PACKAGE LABEL

PACKAGE LABEL - PRINCIPAL DISPLAY - Dilaudid 1 mL Single-Dose Tip Cap Label

Dilaudid® CII

HYDROmorphone HCl

Injection, USP

0.2 mg/mL

For Subcutaneous, IM, or slow IV use.

PACKAGE LABEL

PACKAGE LABEL - PRINCIPAL DISPLAY - Dilaudid 1mL Single-Dose Carton Panel

Rx only 771311 NDC 76045-121-11

Dilaudid® CII

HYDROmorphone HCl

Injection, USP

0.2 mg/mL

For Subcutaneous, Intramuscular, or slow Intravenous use.

Do NOT dilute for IV push.

Do NOT place syringe on a Sterile Field.

10 x 1 mL single-dose prefilled syringes

Discard unused portion.

PACKAGE LABEL

PACKAGE LABEL – PRINCIPAL DISPLAY PANEL – Dilaudid 1 mL Single-Dose Syringe Label

For SC, IM, or slow IV use. 1 mL Single-Dose.

Rx only

Dilaudid® CII

HYDROmorphone HCl

Injection, USP

1 mg/mL

PACKAGE LABEL

PACKAGE LABEL - PRINCIPAL DISPLAY - Dilaudid 1 mL Single-Dose Tip Cap Label

Dilaudid® CII

HYDROmorphone HCl

Injection, USP

1 mg/mL

For Subcutaneous, IM, or slow IV use.

PACKAGE LABEL

PACKAGE LABEL - PRINCIPAL DISPLAY - Dilaudid 1mL Single-Dose Carton Panel

Rx only 771911 NDC 76045-009-11

Dilaudid® CII

HYDROmorphone HCl

Injection, USP

1 mg/mL

For Subcutaneous, Intramuscular, or slow Intravenous use.

Do NOT dilute for IV push.

Do NOT place syringe on a Sterile Field.

10 x 1 mL single-dose prefilled syringes

Discard unused portion.

PACKAGE LABEL

PACKAGE LABEL – PRINCIPAL DISPLAY PANEL – Dilaudid 1 mL Single-Dose Syringe Label

For SC, IM, or slow IV use. 1 mL Single-Dose.

Rx only

Dilaudid® CII

HYDROmorphone HCl

Injection, USP

2 mg/mL

PACKAGE LABEL

PACKAGE LABEL - PRINCIPAL DISPLAY - Dilaudid 1 mL Single-Dose Tip Cap Label
Dilaudid® CII
HYDROmorphone HCl
Injection, USP

2 mg/mL

For Subcutaneous, IM, or slow IV use.

PACKAGE LABEL

PACKAGE LABEL - PRINCIPAL DISPLAY - Dilaudid 1mL Single-Dose Carton Panel
Rx only 771011 NDC 76045-010-11
Dilaudid® CII
HYDROmorphone HCl
Injection, USP

2 mg/mL
For Subcutaneous, Intramuscular, or slow Intravenous use.
Do NOT dilute for IV push.
Do NOT place syringe on a Sterile Field.
10 x 1mL single-dose prefilled syringes
Discard unused portion.